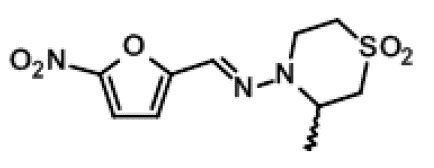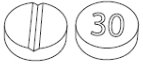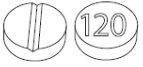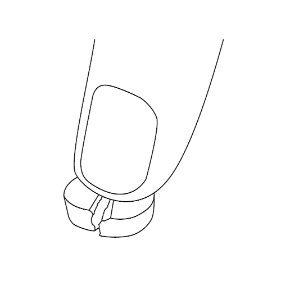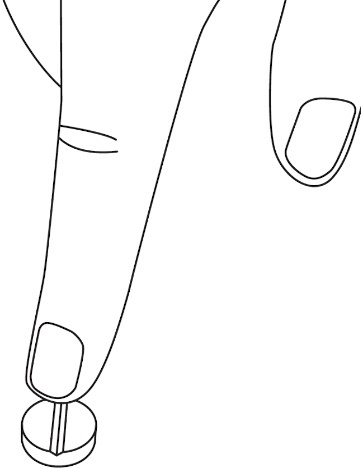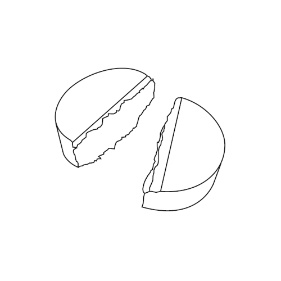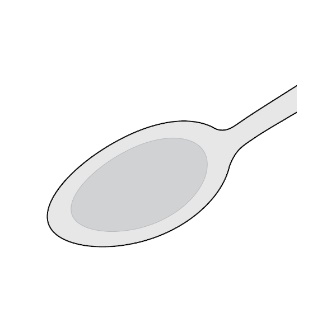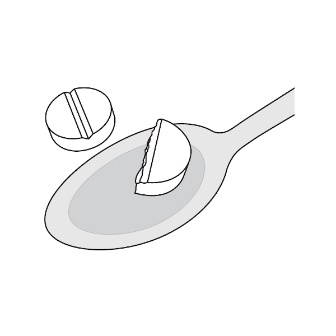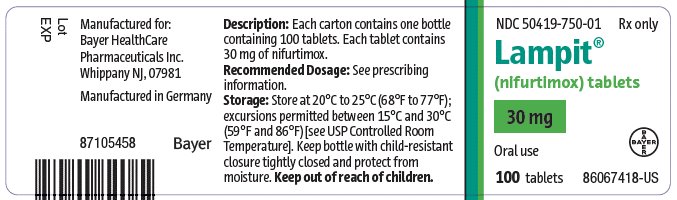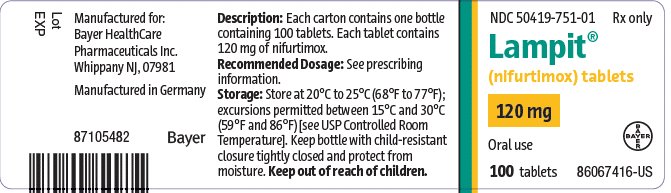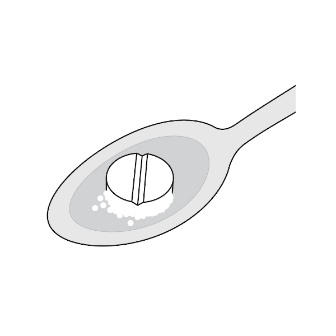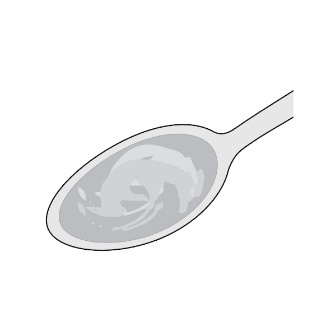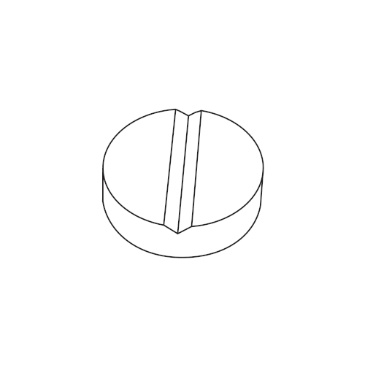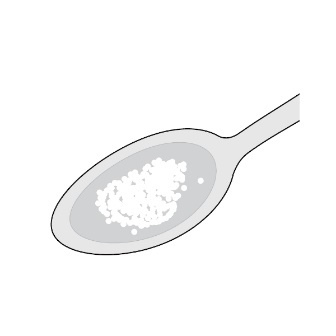 DRUG LABEL: LAMPIT
NDC: 50419-750 | Form: TABLET, FILM COATED
Manufacturer: Bayer Healthcare Pharmaceuticals INC.
Category: prescription | Type: HUMAN PRESCRIPTION DRUG LABEL
Date: 20241210

ACTIVE INGREDIENTS: NIFURTIMOX 30 mg/1 1
INACTIVE INGREDIENTS: DIBASIC CALCIUM PHOSPHATE DIHYDRATE; MAGNESIUM STEARATE; STARCH, CORN; SILICON DIOXIDE; SODIUM LAURYL SULFATE

HIGHLIGHTS OF PRESCRIBING INFORMATION

These highlights do not include all the information needed to use LAMPIT safely and effectively. See full prescribing information for LAMPIT.
LAMPIT (nifurtimox) tablets, for oral use
Initial U.S. Approval: 2020

RECENT MAJOR CHANGES

Warnings and Precautions, Embryo-Fetal Toxicity (5.2) 2/2023

1 INDICATIONS AND USAGE

LAMPIT is a nitrofuran antiprotozoal, indicated in pediatric patients (birth to less than 18 years of age and weighing at least 2.5 kg) for the treatment of Chagas disease (American Trypanosomiasis), caused by Trypanosoma cruzi. (1)

2 DOSAGE AND ADMINISTRATION

- LAMPIT tablets must be taken with food (2.1)

Dosage of LAMPIT in Pediatric Patients
(birtha to less than 18 years of age) (2.2)
Body Weight Group | Total Daily Dose of nifurtimox; (mg/kg)
41 kg or greater | 8 to 10
Less than 41 kg | 10 to 20

aTerm newborn with body weight greater than or equal to 2.5 kg

- Administer LAMPIT tablets orally, three times daily with food for 60 days. (2.2)
- Obtain a pregnancy test in females of reproductive potential prior to initiating treatment with LAMPIT (2.3, 8.3).
- See Full Prescribing Information for additional important administration instructions. (2.1, 2.2, 2.4, 2.5)

3 DOSAGE FORMS AND STRENGTHS

- Tablets: 30 mg (functionally scored) (3)
- Tablets: 120 mg (functionally scored) (3)

4 CONTRAINDICATIONS

- Known hypersensitivity to nifurtimox or to any of the excipients in LAMPIT. (4)
- Alcohol consumption during treatment. (4)

5 WARNINGS AND PRECAUTIONS

- Potential for Genotoxicity and Carcinogenicity. (5.1)
- Embryo-Fetal Toxicity: May cause fetal harm. Pregnancy testing is recommended for females of reproductive potential. Advise females of reproductive potential of the potential risk to a fetus and to use effective contraception. Advise males to use condoms with female partners of reproductive potential. (2.3, 5.2, 8.1, 8.3)
- Worsening Neurological and Psychiatric Conditions: Patients with a history of brain injury, seizures, psychiatric disease, serious behavioral alterations may experience worsening of their conditions when receiving LAMPIT. Administer LAMPIT under close medical supervision in these patients or if neurological disturbances or psychiatric drug reactions occur. (5.3)
- Hypersensitivity: Hypersensitivity reactions including hypotension, angioedema, dyspnea, pruritus, rash or other severe skin reactions have been reported with the use of nifurtimox, discontinuation of treatment is recommended. (5.4)
- Decreased Appetite and Weight Loss: Check body weight every 14 days as dosage may need to be adjusted. (5.5)
- Porphyria: Treatment with nitrofuran derivatives, such as LAMPIT, may precipitate acute attacks of porphyria. Administer LAMPIT under close medical supervision in patients with porphyria. (5.6)

6 ADVERSE REACTIONS

The most frequently reported adverse reactions (≥5%) are vomiting, abdominal pain, headache, decreased appetite, nausea, pyrexia, and rash. (6)

To report SUSPECTED ADVERSE REACTIONS, contact Bayer HealthCare Pharmaceuticals Inc. at 1-888-842-2937 or FDA at 1-800-FDA-1088 or www.fda.gov/medwatch.

8 USE IN SPECIFIC POPULATIONS

Patients with Renal and or Hepatic Impairment: Administer LAMPIT under close medical supervision. (8.6, 8.7)

FULL PRESCRIBING INFORMATION

1 INDICATIONS AND USAGE

LAMPIT is indicated in pediatric patients (birth to less than 18 years of age and weighing at least 2.5 kg) for the treatment of Chagas disease (American Trypanosomiasis) caused by Trypanosoma cruzi [see Clinical Studies (14)].

2 DOSAGE AND ADMINISTRATION

2.1 Important Administration Instructions

- LAMPIT (30 mg and 120 mg) tablets are for oral use and must be taken with food.
- LAMPIT tablets are dosed by body weight of the patient [see Dosage and Administration (2.2)].
- LAMPIT (30 mg and 120 mg) tablets are functionally scored tablets which can be split into one-half (15 mg and 60 mg respectively) at the scored lines by hand. Do not break LAMPIT tablets mechanically with a tablet splitting device [see Dosage and Administration (2.4) and Instructions for Use].
- LAMPIT 30 mg and 120 mg tablets can be made into a slurry as an alternative method of administration for patients who cannot swallow the tablets [see Dosage and Administration (2.5)].
- Discontinue consumption of alcohol during treatment with LAMPIT [see Contraindications (4) and Drug Interactions (7)].
- Complete the full course of treatment to prevent recurrence of the infection.
- If a dose is missed, take the missed dose as soon as possible together with food. However, if it is within 3 hours of the next scheduled dose, skip the missed dose and continue treatment as prescribed. Do not take a double dose to make up for a missed dose.

2.2 Recommended Dosage in Pediatric Patients

- Administer LAMPIT (30 mg and 120 mg) tablets orally three times a day with food.
- Total daily recommended dosages of LAMPIT are based on the body weight of the patient (see Table 1).
- Adjust LAMPIT dosage accordingly if body weight decreases during treatment [see Warnings and Precautions (5.4)].
- The recommended duration of treatment with LAMPIT is 60 days.

Table 1: Total Daily Recommended Dosages of LAMPIT Based on Body Weight

Age | Body weight group | Total daily dose of nifurtimox (mg/kg)
Birtha to less than 18 years | 41 kg or greater | 8 to 10
Birtha to less than 18 years | Less than 41 kg | 10 to 20

aTerm newborn with body weight of greater than or equal to 2.5 kg

Table 2: Individual Dosages Based on Body Weight in Pediatric Patients (Birtha to Less than 18 years of age)

Body weight (kg) | Dose (mg) | Number of LAMPIT 30 mg tablets per dose (3 x Daily) | Number of LAMPIT 120 mg tablets per dose (3 x Daily)
2.5 kg to 4.5 kg | 15 mg | ½ tablet | —
4.6 kg to less than 9 kg | 30 mg | 1 tablet | —
9 kg to less than 13 kg | 45 mg | 1 ½ tablets | —
13 kg to less than 18 kg | 60 mg | 2 tablets | ½ tablet
18 kg to less than 22 kg | 75 mg | 2 ½ tablets | —
22 kg to less than 27 kg | 90 mg | 3 tablets | —
27 kg to less than 35 kg | 120 mg | 4 tablets | 1 tablet
35 kg to less than 41 kg | 180 mg | — | 1 ½ tablets
41 kg to less than 51 kg | 120 mg | — | 1 tablet
51 kg to less than 71 kg | 180 mg | — | 1 ½ tablets
71 kg to less than 91 kg | 240 mg | — | 2 tablets
91 kg or greater | 300 mg | — | 2 ½ tablets

aTerm newborn with body weight of greater than or equal to 2.5 kg

2.3 Pregnancy Testing Prior to Initiating LAMPIT

Obtain a pregnancy test in females of reproductive potential prior to initiating treatment with LAMPIT [see Warnings and Precautions (5.2) and Use in Specific Populations (8.3)].

2.4 Instructions for Splitting LAMPIT Tablets

Do not break LAMPIT tablets mechanically with a tablet splitting device. A functional score line is used to divide the tablet by hand as follows:

- To split LAMPIT tablet, place the tablet on a flat surface with the score line facing up.
- With the tablet resting on the flat surface, apply enough downward pressure with the index finger centered on the top of the tablet to break it along the score line.

2.5 Preparation of a Slurry of LAMPIT as an Alternate Method of Administration

For patients who are unable to swallow whole or half tablets, LAMPIT tablet can be dispersed in water and administered as outlined below.

- Place approximately 2.5 mL of water into a spoon.
- Place the prescribed dose into the water.
- Allow the tablet(s) to disintegrate (typically less than 30 seconds).
- A slurry (liquid suspension) is formed.
- Take the slurry immediately with food.

3 DOSAGE FORMS AND STRENGTHS

LAMPIT tablets are available as 30 mg and 120 mg tablets.

- 30 mg, yellow, round, biconvex tablets, functionally scored on one side for the division of the tablet into equal doses and marked with ‘30’ on the other side.
- 120 mg, yellow, round, biconvex tablets, functionally scored on one side for the division of the tablet into equal doses and marked with ‘120’ on the other side

4 CONTRAINDICATIONS

LAMPIT tablets are contraindicated in:

- Patients with known hypersensitivity to nifurtimox or any of the excipients in LAMPIT [see Warnings and Precautions (5.4)].
- Patients who consume alcohol during treatment [see Drug Interactions (7)]

5 WARNINGS AND PRECAUTIONS

5.1 Potential for Genotoxicity and Carcinogenicity

Genotoxicity

Genotoxicity of LAMPIT has been demonstrated in humans, in vitro in several bacterial species and mammalian cell systems, and in vivo in rodents [see Nonclinical Toxicology (13.1)].

A study evaluating the cytogenetic effect of nifurtimox in pediatric patients ranging from 7 months to 14 years of age with Chagas disease demonstrated a 13-fold increase in chromosomal aberrations.

Carcinogenicity

Carcinogenicity has been observed in mice and rats treated chronically with nitrofuran agents which are structurally similar to nifurtimox. Similar data have not been reported for LAMPIT [see Nonclinical Toxicology (13.1)]. It is not known whether LAMPIT is associated with carcinogenicity in humans.

5.2 Embryo-Fetal Toxicity

Based on findings from animal studies, LAMPIT can cause fetal harm when administered to a pregnant woman. In animal reproduction studies, nifurtimox administered orally to pregnant rats, and rabbits during organogenesis was associated with reduced maternal body weights in rats, and abortions, fetal death, and smaller litter sizes in rabbits at doses approximately equivalent to and 2-times, respectively, the maximum recommended human dose (MRHD) of 10 mg/kg/day. Fetal malformations were observed in pregnant rabbits administered nifurtimox doses less than the MRHD [see Use in Specific Populations (8.1)].

Advise pregnant women of the potential risk to a fetus. Pregnancy testing is recommended for females of reproductive potential prior to initiating treatment with LAMPIT [see Dosage and Administration (2.3)]. Advise females of reproductive potential to use effective contraception during treatment with LAMPIT and for 6 months after the last dose. Advise male patients with female partners of reproductive potential to use condoms during treatment and for 3 months after the last dose of LAMPIT [see Use in Specific Populations (8.1, 8.3) and Clinical Pharmacology (12.3)].

5.3 Worsening of Neurological and Psychiatric Conditions

Patients with a history of brain injury, seizures, psychiatric disease, or serious behavioral alterations may experience worsening of their conditions when receiving LAMPIT. Administer LAMPIT under close medical supervision in these patients and in patients who develop neurological disturbances or psychiatric drug reactions.

5.4 Hypersensitivity

Cases of hypersensitivity have been reported in patients receiving therapy with nifurtimox. The hypersensitivity could be a reaction induced by nifurtimox or an immune response triggered by Chagas disease during treatment. Hypersensitivity reactions could be accompanied by hypotension, angioedema (including laryngeal or facial edema), dyspnea, pruritus, rash or other severe skin reactions. At the first sign of serious hypersensitivity, discontinue treatment with LAMPIT [see Contraindications (4)].

5.5 Decreased Appetite and Weight Loss

Decreased appetite and weight loss were reported in patients treated with LAMPIT in the clinical trials. During treatment with LAMPIT, patients can lose their appetite or experience nausea/vomiting which can result in weight loss. Check body weight every 14 days, as the dosage may have to be adjusted [see Dosage and Administration (2.2)].

5.6 Porphyria

Treatment with nitrofuran derivatives, such as LAMPIT, may precipitate acute attacks of porphyria. Administer LAMPIT tablets under close medical supervision in patients with porphyria.

6 ADVERSE REACTIONS

The following serious or otherwise important adverse reactions are discussed elsewhere in the labeling:

- Potential for Genotoxicity, Carcinogenicity, and Mutagenicity [see Warnings and Precautions (5.1)]
- Worsening of Neurological and Psychiatric Conditions [see Warnings and Precautions (5.3)]
- Hypersensitivity [see Warnings and Precautions (5.4)]
- Decreased Appetite and Weight Loss [see Warnings and Precautions (5.5)]
- Porphyria [see Warnings and Precautions (5.6)]

6.1 Clinical Trials Experience

Because clinical trials are conducted under widely varying conditions, adverse reaction rates observed in the clinical trials of a drug cannot be directly compared to rates in the clinical trials of another drug and may not reflect the rates observed in practice.

The safety data described below reflect exposure to LAMPIT in one prospective, randomized, double-blind trial (Trial 1). 330 pediatric patients with serologic evidence of T. cruzi infection and without Chagas disease-related cardiac or gastrointestinal symptoms were randomly assigned in a 2:1 fashion to a 60-day (n=219) or a 30-day (n=111) LAMPIT treatment regimen and were followed up for one year after end of treatment. LAMPIT was administered three times a day with food using a body weight-based dosing. The median treatment duration was 61 days for subjects in the 60-day regimen. The majority (86.7%) of the study population was ≥2 to <18 years of age at randomization.

Discontinuation of LAMPIT due to adverse reactions occurred in 14 of 330 (4.2%) patients overall, 12 of 219 (5.5%) patients in the 60-day arm, and 2 of 111 (1.8%) patients in the 30-day arm. Adverse reactions were reported for 213 of 330 (64.5%) patients. The proportion of patients with adverse reactions was higher in the 60-day regimen (67.1%) compared with the 30-day regimen (59.5%). Most patients with adverse reactions had mild (76.5%) or moderate (22.0%) reactions.

The most frequently reported adverse reactions in patients treated with LAMPIT for 60 days were vomiting (14.6%), abdominal pain (13.2%), headache (12.8%), decreased appetite (10.5%), nausea (8.2%), pyrexia (7.3%), rash (5.5%).

Adverse reactions occurring in ≥1% of LAMPIT-treated patients are shown in Table 3.

Table 3 Adverse Reactions Reported in (≥1%) Pediatric Patients with Chagas Disease in Trial 1 Treated with LAMPIT for 60 days

System Organ Class | Adverse Reactions | Incidence
Blood and lymphatic system disorders | Anemia; Eosinophilia | 2.7%; 2.3%
Gastrointestinal disorders | Vomiting; Abdominal paina; Nausea; Diarrhea | 14.6%; 13.2%; 8.2%; 4.6%
General disorders and administration site conditions | Pyrexia | 7.3%
Investigations | Weight decreased | 2.7%
Metabolism and nutrition disorders | Decreased appetite | 10.5%
Nervous system disorders | Headache; Dizziness | 12.8%; 2.7%
Skin and subcutaneous tissue disorders | Rashb; Urticaria | 5.5%; 2.3%

a Abdominal pain includes abdominal pain and abdominal pain upper

b Rash includes rash, rash macular, rash maculo-papular, rash morbilliform, and rash papular.

Other adverse reactions occurring in 0.1% to less than 1% of patients treated with LAMPIT for 60 days included asthenia, vertigo, arthralgia, myalgia, paresthesia, tremor, irritability, anxiety, pruritus, fatigue, somnolence, seizure, syncope, neutropenia, leukopenia.

6.2 Postmarketing Experience

The following safety data were derived during postmarketing surveillance of nifurtimox from outside the United States, including literature data for all age groups (pediatric and adult populations). Because these reactions are reported voluntarily from a population of uncertain size, it is not always possible to reliably estimate their frequency or establish a causal relationship to drug exposure.

Table 4: Postmarketing Adverse Reactions Reported in Pediatric and Adult Populations Treated with Nifurtimox

System Organ Class | Adverse Reaction
Immune system disorders | Hypersensitivity reactions, including anaphylaxis
Ear and labyrinth disorders | Vertigo
Skin and subcutaneous tissue disorders | Angioedema; Drug reaction with eosinophilia and systemic symptoms (DRESS)
Musculoskeletal, connective tissue and bone disorders | Muscle weakness
Nervous system disorders | Amnesia; Polyneuropathy
Psychiatric disorders | Apathy; Agitation; Psychotic behavior; Sleep disorder
Blood and lymphatic system disorders | Thrombocytopenia

7 DRUG INTERACTIONS

Concomitant use of LAMPIT with alcohol may increase the incidence and severity of undesirable effects similar to other nitrofurans and nitroheterocyclic compounds. LAMPIT is contraindicated in patients who consume alcohol during treatment [see Dosage and Administration (2.2) Contraindications (4)].

8 USE IN SPECIFIC POPULATIONS

8.1 Pregnancy

Risk Summary

Based on animal studies, LAMPIT may cause fetal harm when administered to a pregnant woman. Published postmarketing reports on nifurtimox use during pregnancy are insufficient to inform a drug-associated risk of birth defects and miscarriage. There are risks to the fetus associated with Chagas disease (see Clinical Considerations).

Nifurtimox administered orally to pregnant rats, and rabbits during organogenesis was associated with reduced maternal body weights in rats, and abortions, reduced maternal weight gain, and reduced numbers of live fetuses in rabbits when nifurtimox was administered orally during organogenesis at doses approximately equal to the MRHD in rats and 2-times the MRHD in rabbits. An increased incidence of a fetal skeletal malformation (fusion of caudal vertebral bodies) occurred in rabbits at nifurtimox doses approximately 0.2 times the MRHD. In a pre-postnatal study, maternal body weights and fetal body weights of first-generation offspring were reduced at doses approximately equal to or 0.5 times the MRHD, respectively, and several male offspring in the nifurtimox treatment groups exhibited slightly small testes at doses ≥0.2 times the MRHD (see Data). Advise pregnant women of the potential risk to a fetus.

There is a pregnancy safety study for LAMPIT. If LAMPIT is administered during pregnancy, or if a patient becomes pregnant while receiving LAMPIT or within six months following the last dose of LAMPIT, healthcare providers should report LAMPIT exposure by calling 1-888-842-2937.

The estimated background risk of major birth defects and miscarriage for the indicated population is unknown. All pregnancies have a background risk of birth defect, loss, or other adverse outcomes. In the U.S. general population, the estimated background risk of major birth defects and miscarriage in clinically recognized pregnancies is 2 to 4% and 15 to 20%, respectively.

Clinical Considerations

Disease-associated Maternal and/or Embryo/Fetal Risk

Published data from case-control and observational studies on chronic Chagas disease during pregnancy are inconsistent in their findings. Some studies showed an increased risk of pregnancy loss, prematurity and neonatal mortality in pregnant women who have chronic Chagas disease while other studies did not demonstrate these findings. Chronic Chagas disease is usually not immediately life-threatening. Since pregnancy findings are inconsistent, treatment of chronic Chagas disease during pregnancy is not recommended due to risk of embryo-fetal toxicity from LAMPIT.

Acute symptomatic Chagas disease is rare in pregnant women; however, symptoms may be serious or life-threatening. If a pregnant woman presents with acute symptomatic Chagas disease, the risks versus benefits of treatment with LAMPIT to the mother and the fetus should be evaluated on a case-by-case basis.

Data

Animal Data

In an embryo-fetal toxicity study in pregnant rats, 15, 30, and 60 mg/kg/day nifurtimox were administered orally during the period of organogenesis (GD 6 to GD 17). Maternal body weights, body weight gain, and food consumption were reduced in the 60 mg/kg/day dose group. Treatment with nifurtimox did not produce fetal toxicity and no nifurtimox-related fetal malformations were observed. No maternal toxicity was observed at 30 mg/kg/day nifurtimox (approximately 0.5 times the MRHD based on body surface area comparison) and no adverse fetal effects were observed at 60 mg/kg/day nifurtimox (approximately equivalent to the MRHD based on body surface area comparison).

In pregnant rabbits orally administered 5, 15, and 60 mg/kg/day nifurtimox during the period of organogenesis (GD 6 to GD 20), the high dose was associated with maternal toxicity including reduced body weights and food consumption, and abortions in 8/20 high-dose dams. The mean number of live fetuses/litter and the percent of live fetuses per total implantations per group were significantly lower in the mid- and high-dose groups compared to the control group. Nifurtimox administration was associated with increased fetal and litter incidences of a skeletal malformation (fusion of caudal vertebral bodies) in fetuses in the low-dose group receiving 5 mg/kg/day (approximately equivalent to 0.2-times the MRHD based on body surface area comparison). No maternal toxicity was observed at 15 mg/kg/day which is approximately equivalent to 0.5 times the MRHD based on body surface area comparison.

In a pre-postnatal study, pregnant female rats were orally administered 15, 30, and 60 mg/kg/day nifurtimox during organogenesis and lactation [GD 6 to lactation day (LD) 21]. Maternal findings included reduced maternal body weights in high-dose dams during gestation and to a lesser degree during lactation. In first-generation offspring, body weights were significantly reduced in males and females in the high-dose group during the lactation and post-lactation periods. Physical development, neurological function, and reproduction of first-generation offspring were not substantially changed in the nifurtimox treatment groups, but 5–20% of male offspring in all the nifurtimox treatment groups exhibited slightly small testes. No adverse maternal effects or fetal effects on first-generation female offspring occurred at 30 mg/kg/day, and no adverse fetal effects on the development of male offspring occurred at 15 mg/kg/day (respectively approximately 0.5- and 0.2-times the MRHD based on body surface area comparison).

8.2 Lactation

Risk Summary

Published literature demonstrates that nifurtimox is present in human breast milk with an estimated infant daily dose of less than 15% of the recommended daily dose for pediatric patients with Chagas disease. There were no reports of adverse effects on the small number of infants who were breastfed by mothers taking nifurtimox. There is no information on the effects of nifurtimox on milk production. Monitor infants exposed to LAMPIT through breast milk for vomiting, rash, decreased appetite, pyrexia and irritability.

The developmental and health benefits of breastfeeding should be considered along with the mother’s clinical need for LAMPIT and any potential adverse effects on the breastfed infant from LAMPIT or from the underlying maternal condition.

8.3 Females and Males of Reproductive Potential

Pregnancy Testing

Pregnancy testing is recommended for females of reproductive potential prior to initiating treatment with LAMPIT.

Contraception

Females

LAMPIT may cause fetal harm when administered to a pregnant woman [see Use in Specific Populations (8.1)]. Advise females of reproductive potential to use effective contraception during treatment with LAMPIT and for 6 months after the final dose.

Males

Due to the potential for genotoxicity, advise male patients with female partners of reproductive potential to use condoms during treatment and for 3 months after the final dose of LAMPIT [see Nonclinical Toxicology (13.1)].

Infertility

Males

Based on findings in rodents, LAMPIT may impair fertility in males of reproductive potential. These effects on fertility were not reversible in 75% of the animals at 11 weeks after dosing [see Nonclinical Toxicology (13.1)].

8.4 Pediatric Use

The safety and effectiveness of LAMPIT have been established for the treatment of Chagas disease (American Trypanosomiasis) caused by Trypanosoma cruzi in pediatric patients from birth to less than 18 years of age weighing at least 2.5 kg. The efficacy of LAMPIT was demonstrated in pediatric patients 0 to 4 years of age in Trial 1 based on seroconversion to negative on lysate ELISA, recombinant ELISA and IHA at 4 years post-treatment compared to untreated patients. The efficacy of LAMPIT in pediatric patients 5 to <18 years of age was extrapolated from efficacy established in the younger pediatric population. Supportive evidence of efficacy was provided by seroconversion to negative on the F29 ELISA [see Clinical Studies (14)].

The safety and effectiveness of LAMPIT has not been established in pediatric patients weighing less than 2.5 kg.

8.6 Renal Impairment

The effect of renal impairment on the pharmacokinetics of nifurtimox is unknown [see Clinical Pharmacology (12.3)]. Published literature suggests that blood concentrations of nifurtimox were increased in patients with End Stage Renal Disease (ESRD) requiring hemodialysis [see, Clinical Pharmacology (12.3)]. Administer LAMPIT under close medical supervision.

8.7 Hepatic Impairment

The effect of hepatic impairment on the pharmacokinetics of nifurtimox is unknown [Clinical Pharmacology (12.3)]. Administer LAMPIT under close medical supervision.

11 DESCRIPTION

LAMPIT contains nifurtimox, an antiprotozoal. The chemical name is (E)-N-(3-Methyl-1,1-dioxidothiomorpholin-4-yl)-1-(5-nitro-2-furyl)methanimine.

The molecular weight is 287.29 and the molecular formula is C10 H13 N3 O5 S. The structural formula is:

LAMPIT (nifurtimox) tablets are yellow round, biconvex tablets, each containing 30 mg or 120 mg of nifurtimox, intended for oral use. The 30 mg tablets are functionally scored on one side and marked with ‘30’ on the other side. The 120 mg tablets are functionally scored on one side and marked with ‘120’ on the other side.

The inactive ingredients of the tablets are as follows: calcium hydrogen phosphate dihydrate, magnesium stearate, maize starch, silica colloidal anhydrous and sodium lauryl sulfate.

12 CLINICAL PHARMACOLOGY

12.1 Mechanism of Action

Nifurtimox is an antiprotozoal drug [see Microbiology (12.4)].

12.2 Pharmacodynamics

Nifurtimox exposure-response relationships and the time course of pharmacodynamics response are unknown.

Cardiac Electrophysiology

At the recommended dose, nifurtimox treatment does not result in large mean increases (>20 ms) in the QTc interval.

12.3 Pharmacokinetics

Absorption

The mean (%CV) nifurtimox AUC estimates ranged between 1676-2670 µg∙h/L (19–32%) and Cmax estimates ranged between 425-568 µg/L (26–50%) following administration of single dose 120 mg nifurtimox with food in adult Chagas patients. No clinically significant differences in nifurtimox AUC or Cmax at the 120 mg dose were observed when using two tablet strengths (30 and 120 mg) or administered as whole or dissolved tablets under fed conditions. The median time to reach maximum concentration (Tmax) of nifurtimox under fed conditions was 4 hours (range: 2 to 8 hours).

Effect of Food

Following administration of a single oral dose of 120 mg LAMPIT in adult Chagas patients, nifurtimox Cmax increased 68%, AUC increased 71%, and Tmax increased by 1 hour with a high-fat meal (800–1000 calorie, approximately 60% fat) compared to fasted conditions.

Distribution

Nifurtimox passes the blood brain barrier as well as the placental barrier. The plasma proteins binding of nifurtimox is 42%.

Elimination

The mean (%CV) estimates for elimination half-life of nifurtimox ranged between 2.4–3.6 hours (12–37%).

Metabolism

Metabolism of nifurtimox is primarily mediated via nitroreductases. Exploratory investigations identified two major pharmacologically inactive metabolites (M-4, M-6) and several other minor metabolites in pooled human plasma. M-4 is a rearranged cysteine conjugate of nifurtimox with a half-life of approximately 28 hours, and M-6 is postulated to be formed by hydrolytic cleavage of the hydrazone moiety with a half-life of approximately 10 hours.

Excretion

Following administration of nifurtimox under fed and fasted conditions, approximately 44% and 27% of the dose was recovered in urine mainly as metabolites, respectively. Biliary and fecal elimination of nifurtimox and its metabolites has not been evaluated.

Specific Populations

The effect of renal or hepatic impairment on the pharmacokinetics of nifurtimox is unknown. Blood concentrations of nifurtimox increased in patients with ESRD.

Drug Interaction Studies

Clinical Studies

No clinical studies evaluating the drug interaction potential of nifurtimox have been conducted.

In Vitro Studies

Cytochrome P450 Enzymes (CYPs): Nifurtimox is not a substrate of CYPs. Nifurtimox and its metabolites (M-4 or M-6) are not inhibitors or inducers of CYPs.

Transporter Systems: Nifurtimox is not a substrate or inhibitor of P-glycoprotein (P-gp) or breast cancer resistant protein (BCRP), and is not an inhibitor of organic anion transporting polypeptide (OATPs), multidrug and toxin extrusion (MATE) proteins (MATE1/MATE2-K), organic anion transporter 1/3 (OAT1/OAT3), or organic cation transporter 2 (OCT2). Major metabolites (M-4 or M-6) of nifurtimox are not inhibitors of P-gp, BCRP, OATPs, MATE1, MATE2K, OAT1, OAT3, or OCT2 at clinically relevant concentrations.

12.4 Microbiology

Mechanism of Action

The mechanism of action of nifurtimox is not fully understood. Studies suggest that nifurtimox is metabolized/activated, by Type I (oxygen insensitive) and Type II (oxygen sensitive) nitoreductases (NTR) leading to production of toxic intermediate metabolites and/or reactive oxygen species that induce DNA damage and cell death of both intracellular and extracellular forms of T. cruzi.

Antimicrobial Activity

Nifurtimox is active against all three stages, trypomastigotes, amastigotes, and epimastigotes, of T. cruzi. However, the sensitivity of T. cruzi strains to nifurtimox, from different geographic regions, may vary.

Resistance

In vitro studies suggest the potential for development of resistance in T. cruzi against nifurtimox.

The mechanism of resistance to nifurtimox appears to be multifactorial. Trypanosomal nitroreductase is defined as a key resistance determinate. Either loss of gene copy, mutation of gene or down-regulation of gene expression are sufficient to cause decreased susceptibility of T. cruzi against nitroheterocyclic drugs like nifurtimox. In addition, other mechanisms of resistance like lower drug influx or higher drug efflux are described. However, the clinical relevance of these findings is not known.

Cross-resistance

Nonclinical studies suggest cross-resistance between nifurtimox and benznidazole. This appears to be due to down regulation of Type I NTR localized in the mitochondria.

13 NONCLINICAL TOXICOLOGY

13.1 Carcinogenesis, Mutagenesis, Impairment of Fertility

Carcinogenicity

Adequate long-term carcinogenicity studies for nifurtimox have not been performed. Nitrofurans, which have similar chemical structures to nifurtimox have been reported to be carcinogenic in mice and rats.

Genetic Toxicity

The genotoxicity of nifurtimox has been demonstrated in vitro in several bacterial species and mammalian cell systems and in vivo in mammals.

Nifurtimox was mutagenic in strains of S. typhimurium (TA 98, 100, and 1537) in an Ames assay.

Nifurtimox was genotoxic in human lymphocytes in an in vitro micronucleus assay.

In vivo, nifurtimox was shown to be positive for genotoxicity in a mouse micronucleus assay, a mouse sister-chromatid exchange assay, and a human chromosome aberration assay. However, in a sister-chromatid exchange study in humans, oral doses of nifurtimox did not cause a significant increase in the frequency of sister-chromatid exchange in blood lymphocytes.

Impairment of Fertility

In a study examining the effects of nifurtimox on testicular morphology, male mice fed 0.08% or 0.16% nifurtimox in animal feed for 14 weeks experienced dose-dependent testicular toxicity including complete inhibition of spermatogenesis with the highest dose, evidence of arrested mitosis, signs of pyknosis, and no mature sperm. However, interstitial cells were unchanged, and fibrosis and inflammatory infiltrates were not observed. Nine weeks after the end of nifurtimox exposure, all testicular effects were almost entirely reversed.

In a male and female fertility study in rats, nifurtimox was administered in dietary feed at doses of 150 ppm (equivalent to 7–15 mg/kg), 300 ppm (equivalent to 15–30 mg/kg/day), and 600 ppm (equivalent to 30–60 mg/kg/day) for 10 weeks before mating. Male fertility was completely inhibited in rats administered 30–60 mg/kg/day nifurtimox, but female fertility was not affected for the same dosing regimen. In a recovery study, 11 weeks after the end of dosing, fertility was still inhibited in 75% of male rats administered nifurtimox for 32 weeks indicating a lack of complete reversibility. The nifurtimox dose in male rats that was not associated with inhibition of fertility was considered to be ≤30 mg/kg/day which is approximately equivalent to 0.5 times the MRHD for fertile males based on body surface area comparison.

14 CLINICAL STUDIES

Clinical Study Overview

The safety and efficacy of LAMPIT for the treatment of Chagas disease in pediatric patients birth to <18 years of age and weighing at least 2.5 kg were demonstrated in one prospective, randomized, double-blind trial conducted in Argentina, Bolivia and Colombia (Trial 1, NCT02625974). This trial consisted of 2 parts, Part 1 which included treatment with LAMPIT and one year post-treatment follow-up and Part 2, which included an additional three-years of follow up.

Trial 1: Treatment with LAMPIT including One Year Post-treatment Follow-up (Part 1)

Pediatric patients (n=330) with serologic evidence of T. cruzi infection and without Chagas disease-related cardiac or gastrointestinal symptoms were randomly assigned in a 2:1 fashion to a 60-day (n=219) or a 30-day (n=111) LAMPIT treatment regimen. Patients were followed up for one year. LAMPIT was administered three times a day with food using the following body weight-based dosing regimens: pediatric patients weighing less than 41 kg received a total daily dose of 10-20 mg/kg, and those weighing 41 kg or more received a total daily dose of 8-10 mg/kg [see Dosage and Administration (2.2)]. Chagas disease diagnosis was confirmed by direct observation of T. cruzi by concentration test in patients <8 months of age at randomization and by demonstrating positive results for both the lysate enzyme-linked immunosorbent assay (ELISA) and the recombinant ELISA in patients ≥8 months to <18 years of age at randomization.

Serological response to treatment was defined as ≥20% decrease in optical density measured by lysate and recombinant ELISA in subjects >8 months to <18 years or seroconversion to negative (defined as negative immunoglobulin G concentration in all patients) at 1-year post-treatment follow-up.

The results for both the lysate ELISA and the recombinant ELISA (Table 5) showed superiority in favor of the LAMPIT 60-day arm compared to the LAMPIT 30-day arm (not an approved dosing regimen).

Table 5: Efficacy Results using Lysate ELISA and Recombinant ELISA at 1 year Post-Treatment

 | Lysate ELISA |  | Recombinant ELISA
 | 60-Day; N=219 | 30-Day*; N=111 | 60-Day; N=219 | 30-Day*; N=111
Serological Response | 70 (32%) | 21 (19%) | 76 (35%) | 24 (22%)
≥ 20% decrease in optical density | 59 (27%) | 15 (14%) | 65 (30%) | 17 (15%)
Seroconversion | 11 (5%) | 6 (5%) | 11 (5%) | 7 (6%)
Difference (60 day – 30 day), 95% CI, p-value | 13% (3.5%, 22.6%), 0.007 |  | 13% (3.2%, 23.0%), 0.010
CI=confidence interval
*The 30-day duration is not an approved dosing regimen.

The F29 ELISA detects antibodies to recombinant antigens obtained from the flagellar protein F29 of T. cruzi. Of the 214 patients who were seropositive for the assay at baseline, 46 of 142 (32.4%) in the 60-day LAMPIT treatment arm and 20 of 72 (27.8%) in the 30-day LAMPIT treatment arm (not an approved dosing regimen) seroconverted to negative at the 1-year post-treatment follow-up. Twenty of 59 (33.9%, 95% CI: 22.1%, 47.4%) patients between 6 and 12 years of age in the 60-day arm seroconverted to negative at the 1-year post-treatment follow-up. A similar seroconversion rate was observed in patients 6 and 12 years of age in the 30-day treatment arm. These rates were higher than the 2.8% conversion rate from historical data^1 for untreated patients between 6 and 12 years old at 12 months using the F29 ELISA.

Trial 1: Additional Three-years of Follow-up (Part 2)

To determine the seroconversion rate in patients treated with LAMPIT at the 4-year time point, a total of 295 (197 in the 60-day regimen and 98 in the 30-day regimen) of the 330 pediatric patients were followed for another 3 years after the end of Part 1. Seroconversion to negative confirmed by three assays, lysate ELISA, recombinant ELISA and IHA, was evaluated in patients in the 60-day treatment arm by age group (Table 6) in Part 2. Patients were considered as seroconverted to negative if all three test results were negative. All seroconversions at 4 years post-treatment were from patients who were <2 years of age at baseline. Nine of 11 (81.8%) patients in the 60-day treatment arm who were <8 months of age at baseline seroconverted to negative at 4 years post-treatment. Among 39 patients in the 60-day treatment arm who were 0 to 4 years of age at baseline, 9 (23.1%) seroconverted for 2 or more consecutive years, which was higher than the 0% conversion rate from historical data^2 for untreated patients infected between 0 and 4 years of age during long-term follow-up.

Table 6: Efficacy Results using Seroconversion to Negative Confirmed by Lysate ELISA, Recombinant ELISA and IHA at 4 years Post-Treatment

Age Group | 60-Day; N=197; n (%)
0 to <8 months* | 9/11 (81.8%)
8 months to <2 years | 3/15 (20.0%)
2 to 17 years | 0/171

* A positive T. cruzi concentration test was required for subjects <8 months of age at baseline for enrollment

The efficacy of LAMPIT in pediatric patients 5 to <18 years of age was extrapolated from efficacy established in the younger pediatric population between 0 and 4 years of age. Biologically, it is expected that LAMPIT would have the same effect on T. cruzi in all pediatric age groups. The pathogenesis of Chagas disease is the same across the pediatric population; however, older patients may have a longer duration of infection than younger patients. Given longer duration of infection, time to seroconversion is expected to be longer. Based on published studies, younger pediatric patients seroconvert faster.^2,3 The lack of seroconversion to negative on traditional assays in older pediatric patients in Trial 1 is not unexpected given the duration of follow up of 4 years. It is expected that seroconversion rates would increase in older pediatric age groups over time. Supportive evidence of efficacy was provided by data on seroconversion to negative by the F29 ELISA.

15 REFERENCES

1. Sosa Estani, S., E. L. Segura, A. M. Ruiz, E. Velazquez, B. M. Porcel and C. Yampotis (1998) Efficacy of chemotherapy with benznidazole in children in the indeterminate phase of Chagas' disease. Am J Trop Med Hyg 59(4): 526-529.

2. Suasnábar S, Olivera LV, Arias E, Bizai ML, Bottasso O, Arias E, Fabbro D (2021) Trypanocidal therapy among children infected by Trypanosoma cruzi. Serological and electrocardiographic changes over a mean twenty-five-years follow-up period. Acta Tropica 222:106050.

3. Streiger ML, del Barco ML, Fabbro DL, Arias ED, Amicone NA (2004) Longitudinal study and specific chemotherapy in children with chronic Chagas' disease, residing in a low endemicity area of Argentina. Rev Soc Bras Med Trop 37(5):365-375.

16 HOW SUPPLIED/STORAGE AND HANDLING

16.1 How Supplied

LAMPIT tablets are supplied as follows:

- 30 mg, yellow, round, biconvex tablets, functionally scored on one side and marked with ‘30’ on the other side.
- 120 mg, yellow, round, biconvex tablets, functionally scored on one side and marked with ‘120’ on the other side.

LAMPIT tablets 30 mg are supplied as bottles of 100 tablets with child-resistant closures (NDC 50419-750-01).

LAMPIT tablets 120 mg are supplied as bottles of 100 tablets with child-resistant closures (NDC 50419-751-01).

16.2 Storage and Handling

Store at controlled room temperature 20°C to 25°C (68°F to 77°F); excursions permitted to 15°C to 30°C (59°F to 86°F). [See USP Controlled Room Temperature].

Store LAMPIT tablets in the original bottle with child-resistant closures and do not remove the desiccant.

Keep bottle with child-resistant closures tightly closed and protect from moisture.

17 PATIENT COUNSELING INFORMATION

Advise patients to read the FDA-approved patient labeling (Patient Information and Instructions for Use).

Embryo Fetal Toxicity

- Advise pregnant women and females of reproductive potential of the potential risk of LAMPIT to a fetus and to inform their healthcare provider of a known or suspected pregnancy [see Warnings and Precautions (5.2), Use in Specific Populations (8.1, 8.3) and Nonclinical Toxicology (13.1)].
- Advise females of reproductive potential to use effective contraception while taking LAMPIT and for 6 months after the last dose [see Use in Specific Populations (8.3) and Nonclinical Toxicology (13.1)].
- Advise male patients with female partners of reproductive potential to use condoms during treatment with LAMPIT and for 3 months after the final dose of LAMPIT [see Use in Specific Populations (8.3) and Nonclinical Toxicology (13.1)].

Lactation

Advise nursing mothers to monitor infants exposed to LAMPIT through breast milk for vomiting, rash, decreased appetite, fever, and irritability [Use in Specific Populations (8.2)].

Infertility

Advise males of reproductive potential that LAMPIT may impair fertility [see Use in Specific Populations (8.3) and Nonclinical Toxicology (13.1)].

Worsening of Neurological and Psychiatric Conditions

Advise patients with a history of brain injury, seizures, psychiatric disease, serious behavioral alterations or if neurological and/or psychiatric drug reactions occur, that LAMPIT tablets should be administered only under close medical supervision [see Warnings and Precautions (5.1)].

Hypersensitivity

Inform patients that hypersensitivity could be a reaction caused by LAMPIT or an immune response triggered by Chagas disease during treatment. Hypersensitivity reactions could include hypotension, angioedema (including laryngeal or facial edema), dyspnea, pruritus, rash or other severe skin reactions [see Warnings and Precautions (5.2)].

Alcohol Consumption

Advise patients to discontinue alcohol use during treatment with LAMPIT. LAMPIT is contraindicated in patients who consume alcohol during treatment [see Contraindications (4)].

Decreased Appetite and Weight Loss

Inform patients that LAMPIT can cause decreased appetite and weight loss. Body weight should be checked every 14 days, as the dosage may have to be adjusted [see Warnings and Precautions (5.5)].

Porphyria

Advise patients with porphyria that treatment with nitrofuran derivatives, such as LAMPIT, may precipitate acute attacks of porphyria. Administer LAMPIT tablets under close medical supervision in patients with porphyria. [see Warnings and Precautions (5.6)].

Important Administration Instructions

Advise patients to take LAMPIT with food.

Advise patients not to break LAMPIT tablets mechanically with a tablet splitting device [see Dosage and Administration (2.4)].

For patients who cannot swallow tablets, LAMPIT can be dispersed in water and administered as a slurry, taken with food [see Dosage and Administration (2.1, 2.2, 2.5)].

Ability to Operate Vehicles or Machinery

Inform patients that if muscle weakness or tremors occur during treatment with LAMPIT they should not drive, cycle or use any tools or machines [see Adverse Reactions (6.1].

Manufactured for:

Bayer HealthCare Pharmaceuticals Inc., Whippany, NJ 07981 USA

© 2023 Bayer HealthCare Pharmaceuticals Inc.

For more information, call Bayer HealthCare Pharmaceuticals Inc. at Bayer at 1-888-842-2937 or go to www.LAMPIT.com

Patient Package Insert

PATIENT INFORMATION
LAMPIT® (LAM-pit)
(nifurtimox)
tablets, for oral use

What is LAMPIT?
LAMPIT is a prescription medicine used to treat Chagas disease caused by the parasite Trypanosoma cruzi in children less than 18 years of age weighing at least 5.5 pounds (2.5 kg).

It is not known if LAMPIT is safe and effective in children weighing less than 5.5 pounds (2.5 kg).

Do not take LAMPIT if you:

- are allergic to nifurtimox, or any of the ingredients in LAMPIT. See the end of this Patient Information leaflet for a complete list of ingredients in LAMPIT.
- plan to drink alcohol during treatment with LAMPIT.

Before taking LAMPIT, tell your healthcare provider about all your medical conditions, including if you:

- have a history of brain injury, seizures, mental health problems, or behavior changes.
- have kidney problems or are on dialysis.
- have liver problems.
- have a genetic problem called porphyria. Taking LAMPIT can make your symptoms of porphyria including dark urine, severe stomach pain, muscle pain, tingling, numbness, mental changes or skin sensitivity to light worse.
- are pregnant, plan to become pregnant, or think you may be pregnant. LAMPIT can harm your unborn baby.

For females who are able to become pregnant:

- Your healthcare provider should do a pregnancy test before you start taking LAMPIT to make sure that you are not pregnant.
- You should use effective forms of birth control during treatment with LAMPIT and for 6 months after your last dose of LAMPIT. Talk to your healthcare provider about what forms of birth control may be right for you.
- Call your healthcare provider right away if you become pregnant or think you are pregnant during treatment with LAMPIT.

For males:

- LAMPIT may cause fertility problems in males. This may affect your ability to father a child. Talk to your healthcare provider if you have concerns about fertility.
- You should use a condom with female partners who are able to become pregnant, during treatment with LAMPIT and for 3 months after your last dose of LAMPIT.
- are breastfeeding or plan to breastfeed. LAMPIT can pass into breast milk and may harm your baby. Talk to your healthcare provider about the best way to feed your baby during treatment with LAMPIT. If you take LAMPIT and breastfeed, monitor your baby for vomiting, rash, decreased appetite, fever, and irritability.

Tell your healthcare provider about all the medicines you take, including prescription and over-the-counter medicines, vitamins, and herbal supplements.

Know the medicines you take. Keep a list of them with you to show to your healthcare provider and pharmacist when you get a new medicine.

How should I take LAMPIT?

See the detailed Instructions for Use that comes with LAMPIT for information about how to split LAMPIT tablets and how to take LAMPIT if whole tablets or half tablets cannot be swallowed.

- Take LAMPIT exactly as your healthcare provider tells you.
- Your healthcare provider may change your dose if needed.
- Take your prescribed dose of LAMPIT 3 times a day with food.
- LAMPIT tablets are marked with a scored line. LAMPIT tablets can be taken whole or split at the scored line.
- LAMPIT tablets should be split by hand at the scored line. Do not split LAMPIT tablets using a tablet splitting device.
- If you cannot swallow LAMPIT tablets or you are giving LAMPIT to a child who cannot swallow the tablets, be sure to read the Instructions for Use that come with LAMPIT. LAMPIT tablets can be dissolved in water if whole tablets or half tablets cannot be swallowed.
- If you miss a dose of LAMPIT, take it as soon as possible with food. If it is within 3 hours of your next scheduled dose, skip the missed dose and take the next dose at your regular time. Do not take 2 doses to make up for a missed dose.

What are the possible side effects of LAMPIT?

LAMPIT may cause serious side effects, including:

- Worsening of symptoms related to brain injury, seizures, mental health problems or behavior changes in people with a history of these problems. Call your healthcare provider right away if any of these problems get worse during treatment with LAMPIT.
- Allergic reactions. Allergic reactions can happen when taking nifurtimox, the active ingredient in LAMPIT, or with changes in your immune system caused by Chagas disease during treatment with LAMPIT. These allergic reactions can include low blood pressure, swelling of the face and tongue (angioedema), shortness of breath, itching, rash or other skin problems. Call your healthcare provider or get emergency medical help if you get any of these signs and symptoms of an allergic reaction during treatment with LAMPIT.
- Loss of appetite and weight loss. Your healthcare provider should check your weight every 14 days to see if your dose of LAMPIT may need to be changed.

The most common side effects of LAMPIT include:

- vomiting
- abdominal pain
- headache
- decreased appetite
- nausea
- fever
- rash

These are not all the possible side effects of LAMPIT.

Call your doctor for medical advice about side effects. You may report side effects to FDA at 1-800-FDA-1088.

How should I store LAMPIT?

- Store LAMPIT at room temperature between 68°F to 77°F (20°C to 25°C).
- Keep LAMPIT in the bottle that it comes in with the child-resistant cap on the bottle. Do not remove the packet that helps to keep your medicine dry (desiccant).
- Keep the bottle tightly closed and protect from moisture.

Keep LAMPIT and all medicines out of the reach of children.

General information about the safe and effective use of LAMPIT.

Medicines are sometimes prescribed for purposes other than those listed in a Patient Information leaflet. Do not use LAMPIT for a condition for which it was not prescribed. Do not give LAMPIT to other people, even if they have the same symptoms that you have. It may harm them.

You can ask your healthcare provider or pharmacist for information about LAMPIT that is written for health professionals.

What are the ingredients in LAMPIT?
Active ingredient: nifurtimox

Inactive ingredients: calcium hydrogen phosphate dihydrate, magnesium stearate, maize starch, silica colloidal anhydrous, and sodium lauryl sulfate.

Manufactured for: Bayer HealthCare Pharmaceuticals Inc., Whippany, NJ 07981 USA

© 2023 Bayer HealthCare Pharmaceuticals Inc.

For more information, call Bayer HealthCare Pharmaceuticals Inc. at Bayer at 1-888-842-2937 or go to www.LAMPIT.com

This Patient Information has been approved by the U.S. Food and Drug Administration Issued:5/2023

Instructions for Use

LAMPIT (LAM-pit)
(nifurtimox)
tablets, for oral use

This Instructions for Use contains information on how to split LAMPIT tablets and how to prepare a tablet and water mixture (called a slurry) if whole tablets or half tablets cannot be swallowed. Read this Instructions for Use before you start taking LAMPIT and each time you get a refill. There may be new information. This information does not take the place of talking to your healthcare provider about your medical condition or treatment.

LAMPIT 30 mg tablets

LAMPIT 120 mg tablets

Important Information You Need to Know Before Taking LAMPIT

- Do not take more LAMPIT than prescribed by your healthcare provider.
- Take LAMPIT with food.
- Split LAMPIT tablets by hand. Do not split LAMPIT tablets using a tablet splitting device. See the instructions below for splitting tablets by hand.
- If you cannot swallow LAMPIT tablets or you are giving LAMPIT to a child who cannot swallow the tablets, you can dissolve the tablet in water and give the mixture with food. See the instructions below for preparing a tablet and water mixture (slurry).

How to Take LAMPIT

- Take LAMPIT 3 times a day with food.
- Your healthcare provider may need to change your dose of LAMPIT during treatment as needed. Take your LAMPIT dose exactly as prescribed by your healthcare provider.
- LAMPIT 30 mg tablets and 120 mg tablets have a scored line on one side and can be taken whole or broken at the scored line.
- If you miss a dose of LAMPIT, take the missed dose as soon as possible with food. If it is within 3 hours of the next scheduled dose, skip the missed dose and take the next dose at your regular time. Do not take 2 doses to make up for a missed dose.

How to Split LAMPIT Tablets by Hand

Step 1: To split the tablet, place the tablet on a flat surface with the scored line facing up (See Figure A).

Figure A

Step 2: With the tablet still on the flat surface, apply enough pressure down on the center of the tablet with your index finger to split it in half along the scored line (See Figure B).

Figure B

Step 3: LAMPIT tablets can be split in half along the scored line (See Figure C).

Figure C

Step 4: Only use a tablet that has been broken at the scored line (See Figure D).

Figure D

Do not split LAMPIT tablets in any other way.

Preparing a Tablet and Water Mixture (Slurry)

For people who are not able to swallow whole tablets or half tablets, LAMPIT can be mixed in water.

Step 1: Place approximately one-half teaspoonful (2.5 ml) of water into a spoon (See Figure E).

Figure E

Step 2: Place the prescribed dose into the water (See Figure F).

Figure F

Step 3: Allow the tablet to dissolve in the water. This should take less than 30 seconds (See Figure G).

Figure G

Step 4: A tablet and water mixture (slurry) will form (See Figure H).

Figure H

Give the tablet and water mixture (slurry) right away with food. Do not mix more than the prescribed dose.

Storing LAMPIT

- Store LAMPIT at room temperature between 68°F to 77°F (20°C to 25°C).
- Keep LAMPIT in the bottle with child-resistant cap that it comes with. Do not remove the packet that helps to keep your medicine dry (desiccant).
- Keep the bottle tightly closed and protect from moisture.

Keep LAMPIT and all medicines out of the reach of children.

This Instructions for Use has been approved by the U.S. Food and Drug Administration.

Manufactured for:

Bayer HealthCare Pharmaceuticals Inc., Whippany, NJ 07981 USA

© 2020 Bayer HealthCare Pharmaceuticals Inc.

For more information, call Bayer HealthCare Pharmaceuticals Inc. at Bayer at 1-888-842-2937 or go to www.LAMPIT.com

Issued: 8/2020

PACKAGE/LABEL PRINCIPAL DISPLAY PANEL

NDC 50419-750-01

Rx only

Lampit

(nifurtimox) tablets

30 mg

Oral use

100 tablets

PACKAGE/LABEL PRINCIPAL DISPLAY PANEL

NDC 50419-751-01

Rx only

Lampit

(nifurtimox) tablets

120 mg

Oral use

100 tablets